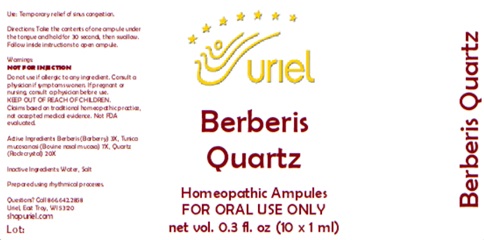 DRUG LABEL: Berberis Quartz
NDC: 48951-2054 | Form: LIQUID
Manufacturer: Uriel Pharmacy Inc.
Category: homeopathic | Type: HUMAN OTC DRUG LABEL
Date: 20260116

ACTIVE INGREDIENTS: BERBERIS VULGARIS ROOT BARK 3 [hp_X]/1 mL; BOS TAURUS NASAL MUCOSA 7 [hp_X]/1 mL; SILICON DIOXIDE 20 [hp_X]/1 mL
INACTIVE INGREDIENTS: WATER; SODIUM CHLORIDE

Berberis Quartz

PURPOSE

Use: Temporary relief of sinus congestion.

INDICATIONS AND USAGE

FOR OARL USE ONLY

DOSAGE AND ADMINISTRATION

Directions: Take the contents of one ampule under the tongue and hold for 30 seconds, then swallow. Follow inside instructions to open ampule.

Warnings:
Do not use if allergic to any ingredient. Consult a physician if symptoms worsen. If pregnant or nursing, consult a physician before use.
KEEP OUT OF REACH OF CHILDREN.
Claims based on traditional homeopathic practice, not accepted medical evidence. Not FDA evaluated.

KEEP OUT OF REACH OF CHILDREN.

ACTIVE INGREDIENT

Active Ingredients: Berberis (Barberry) 3X, Tunica mucosa nasi (Bovine nasal mucosa) 7X, Quartz (Rock crystal) 20X

Inactive Ingredients: Water, Salt

"prepared using rhythmical processes"

Questions? Call 866.642.2858
Uriel, East Troy, WI 53120
shopuriel.com Lot: